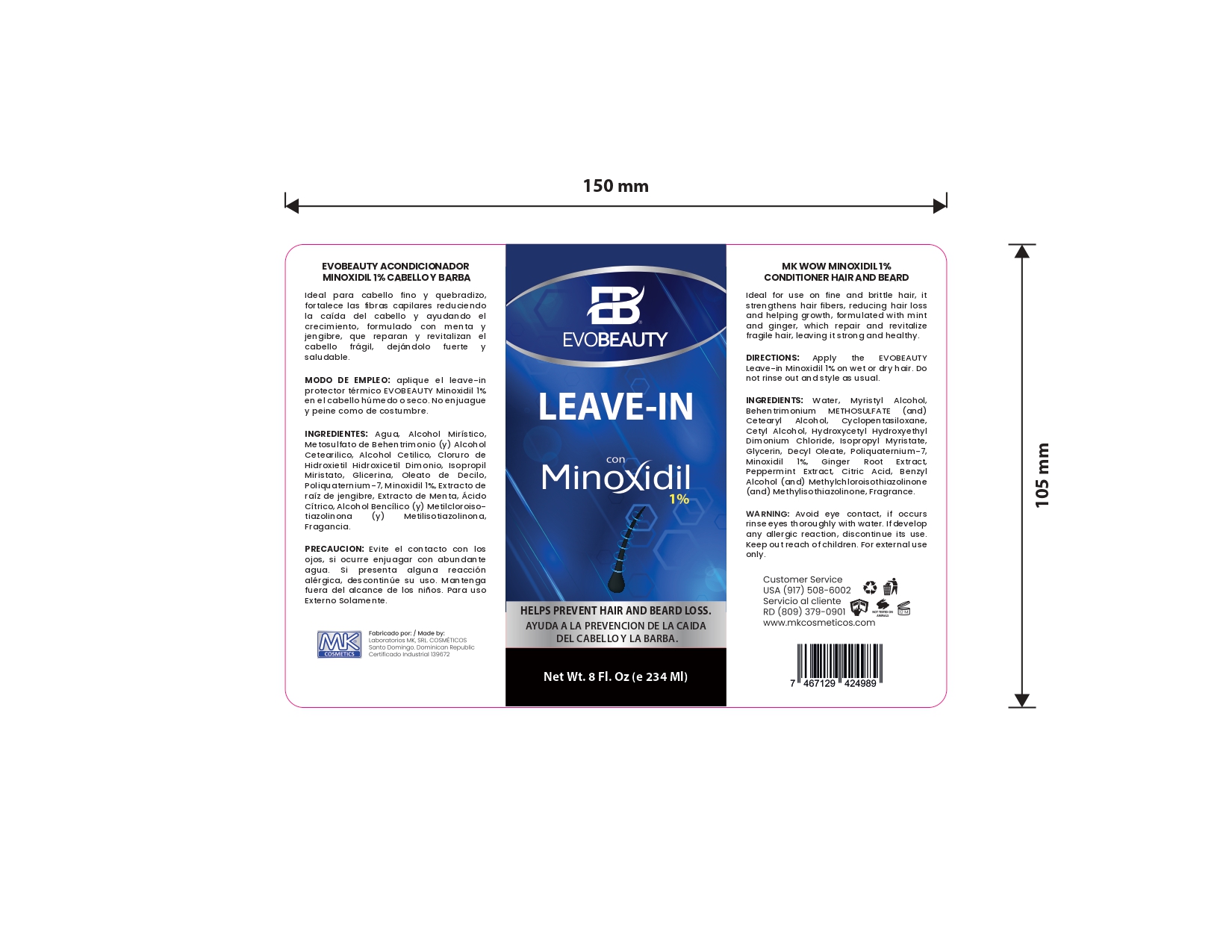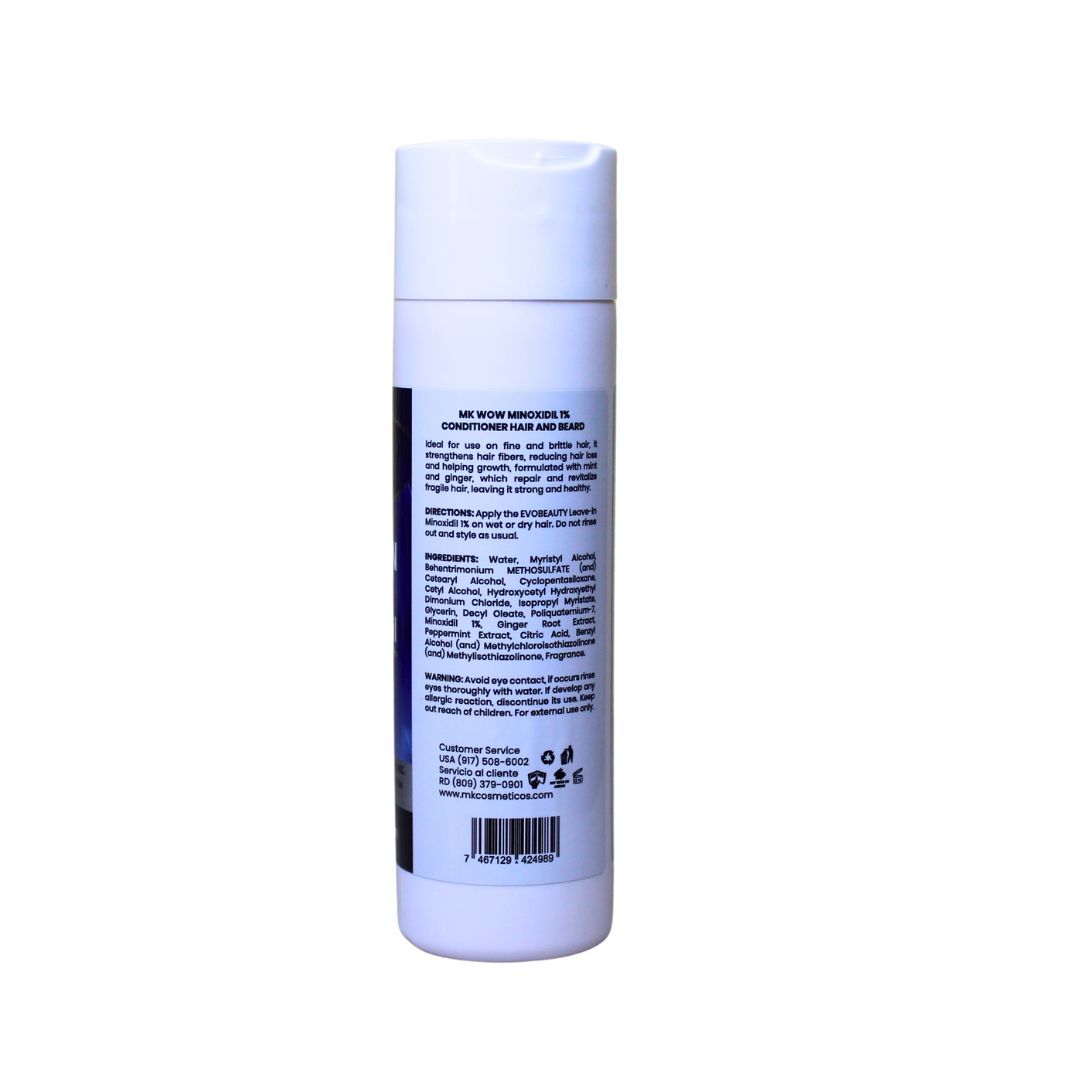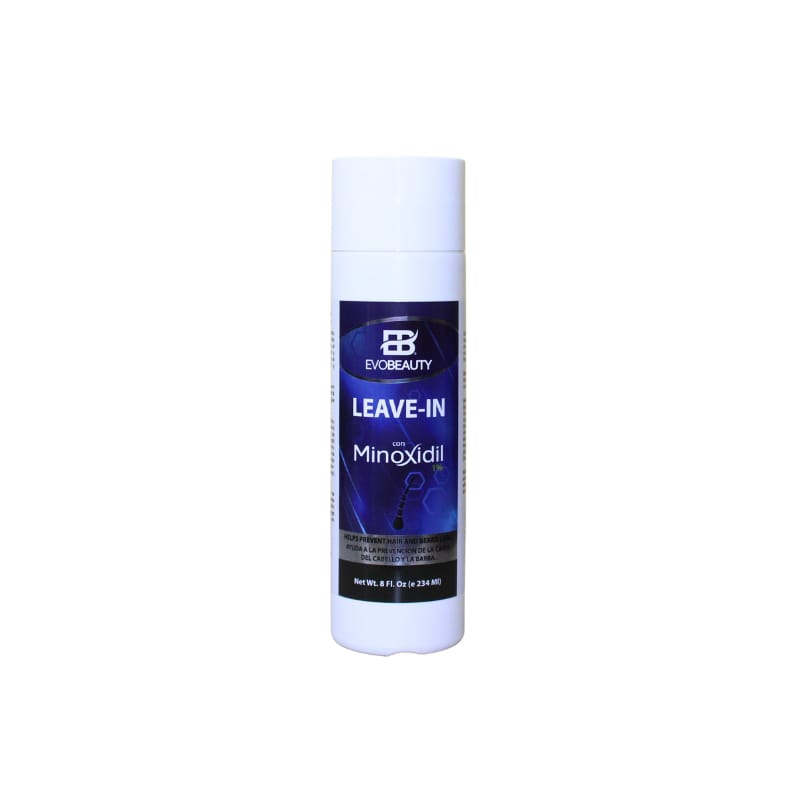 DRUG LABEL: hair leave in
NDC: 87022-010 | Form: CREAM
Manufacturer: LABORATORIO MK SRL
Category: otc | Type: HUMAN OTC DRUG LABEL
Date: 20250829

ACTIVE INGREDIENTS: MINOXIDIL 1 mg/234 mL
INACTIVE INGREDIENTS: GLYCERIN; CETEARYL ALCOHOL; CETYL ALCOHOL; .ALPHA.,.ALPHA.-DIMETHYLBENZYL ALCOHOL; PEPPERMINT; BEHENTRIMONIUM METHOSULFATE; ISOPROPYL MYRISTATE; HYDROXYCETYL HYDROXYETHYL DIMONIUM CHLORIDE; MYRISTYL ALCOHOL; CITRIC ACID; DECYL OLEATE; GINGER; WATER; CYCLOPENTASILOXANE; METHYLCHLOROISOTHIAZOLINONE; POLYQUATERNIUM-7; METHYLISOTHIAZOLINONE

INDICATIONS AND USAGE

Apply the EVOBEAUTY Leave-in Minoxidil 1% on wet or dry hair. Do not rinse out and style as usual.

INACTIVE INGREDIENT

Water, Myristyl Alcohol, Behentrimonium METHOSULFATE (and) Cetearyl Alcohol, Cyclopentasiloxane, Cetyl Alcohol, Hydroxycetyl Hydroxyethyl Dimonium Chloride, Isopropyl Myristate, Glycerin, Decyl Oleate, Polyquaternium-7, Ginger Root Extract, Peppermint Extract, Citric Acid, Benzyl Alcohol (and) Methylchloroisothiazolinone (and) Methylisothiazolinone

WARNINGS

Avoid eye contact, if occurs rinse eyes thoroughly with water. If develop any allergic reaction, discontinue its use.

INFORMATION FOR OWNERS/CAREGIVERS

Customer Service USA (917)508-6002

Customer Service RD (809)379-0900

www.mkcosmeticos.com

DOSAGE AND ADMINISTRATION

Apply the EVOBEAUTY Leave-in Minoxidil 1% on wet or dry hair. Do not rinse out and style as usual.

KEEP OUT OF REACH OF CHILDREN

Keep out reach of children. For external use only.

PURPOSE

growth and help prevent hair and beard loss. Revitalizes hair follicles and stimulates growth.

PACKAGE LABEL

This is the principal panel display side of the minoxidil hair leave in 1%.